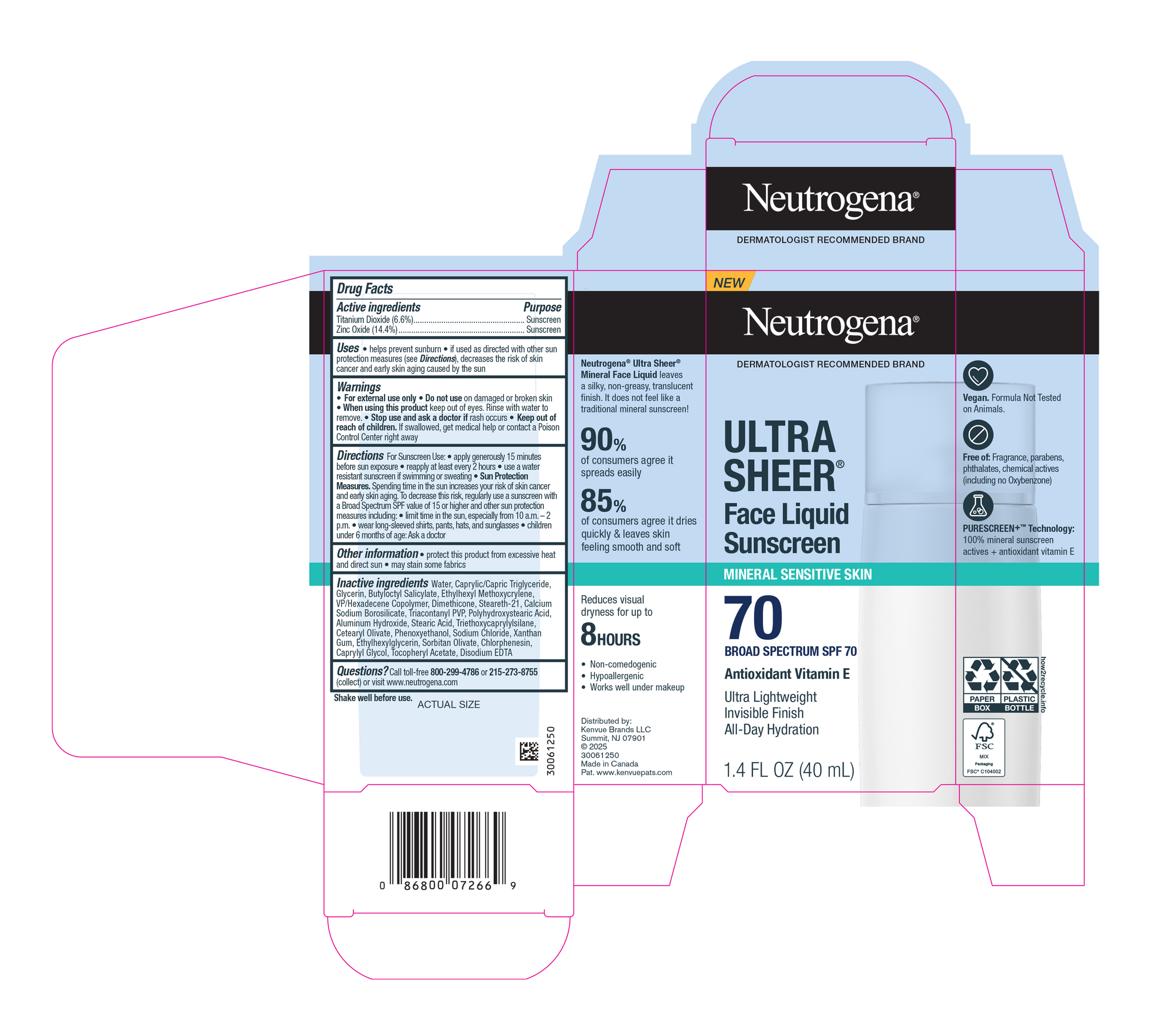 DRUG LABEL: Neutrogena Mineral Ultra Sheer Face SPF 70
NDC: 69968-0895 | Form: LOTION
Manufacturer: Kenvue Brands LLC
Category: otc | Type: HUMAN OTC DRUG LABEL
Date: 20250728

ACTIVE INGREDIENTS: ZINC OXIDE 144 mg/1 mL; TITANIUM DIOXIDE 66 mg/1 mL
INACTIVE INGREDIENTS: XANTHAN GUM; POLYHYDROXYSTEARIC ACID (2300 MW); CAPRYLYL GLYCOL; PHENOXYETHANOL; GLYCERIN; ETHYLHEXYL METHOXYCRYLENE; VINYLPYRROLIDONE/HEXADECENE COPOLYMER; DIMETHICONE; TRIETHOXYCAPRYLYLSILANE; CETEARYL OLIVATE; CHLORPHENESIN; STEARIC ACID; SODIUM CHLORIDE; ETHYLHEXYLGLYCERIN; ALUMINUM HYDROXIDE; BUTYLOCTYL SALICYLATE; TRICONTANYL POVIDONE; CALCIUM SODIUM BOROSILICATE; SORBITAN OLIVATE; MEDIUM-CHAIN TRIGLYCERIDES; .ALPHA.-TOCOPHEROL ACETATE; EDETATE DISODIUM; STEARETH-21; WATER

Neutrogena Mineral Ultra Sheer Face Liquid SPF 70

Drug Facts

ACTIVE INGREDIENT

Active ingredients | Purpose
Titanium Dioxide (6.6%); Zinc Oxide (14.4%) | Sunscreen; Sunscreen

Uses

- helps prevent sunburn
- if used as directed with other sun protection measures (see Directions), decreases the risk of skin cancer and early skin aging caused by the sun

Warnings

For external use only

Do not use on damaged or broken skin

When using this product keep out of eyes. Rinse with water to remove.

Stop use and ask a doctor if rash occurs

Keep out of reach of children. If swallowed, get medical help or contact a Poison Control Center right away

Directions

For Sunscreen Use:

- apply generously 15 minutes before sun exposure
- reapply at least every 2 hours
- use a water resistant sunscreen if swimming or sweating
- Sun Protection Measures. Spending time in the sun increases your risk of skin cancer and early skin aging. To decrease this risk, regularly use a sunscreen with a Broad Spectrum SPF value of 15 or higher and other sun protection measures including:
- limit time in the sun, especially from 10 a.m. – 2 p.m.
- wear long-sleeved shirts, pants, hats, and sunglasses
- children under 6 months of age: Ask a doctor

Other information

- protect this product from excessive heat and direct sun
- may stain some fabrics

Inactive ingredients

Water, Caprylic/Capric Triglyceride, Glycerin, Butyloctyl Salicylate, Ethylhexyl Methoxycrylene, VP/Hexadecene Copolymer, Dimethicone, Steareth-21, Calcium Sodium Borosilicate, Triacontanyl PVP, Polyhydroxystearic Acid, Aluminum Hydroxide, Stearic Acid, Triethoxycaprylylsilane, Cetearyl Olivate, Phenoxyethanol, Sodium Chloride, Xanthan Gum, Ethylhexylglycerin, Sorbitan Olivate, Chlorphenesin, Caprylyl Glycol, Tocopheryl Acetate, Disodium EDTA

Questions?

Call toll-free 800-299-4786 or 215-273-8755 (collect) or visit www.neutrogena.com

Distributed by:

Kenvue Brands LLC

Summit, NJ 07901

PRINCIPAL DISPLAY PANEL - 40 mL Carton Label

NEW

Neutrogena®

DERMATOLOGIST RECOMMENDED BRAND

ULTRA

SHEER®

Face Liquid

Sunscreen

MINERAL SENSITIVE SKIN

70

BROAD SPECTRUM SPF 70

Antioxidant Vitamin E

Ultra Lightweight

Invisible Finish

All-Day Hydration

1.4 FL OZ (40 mL)